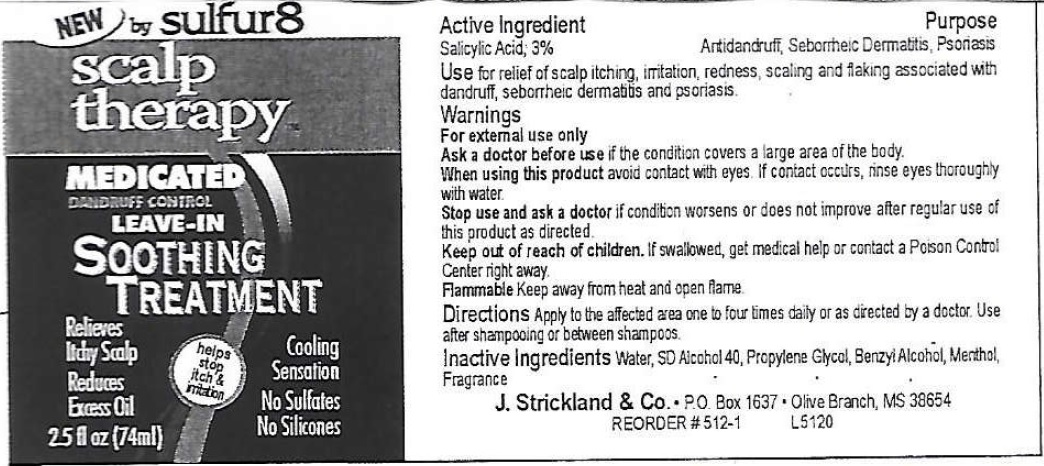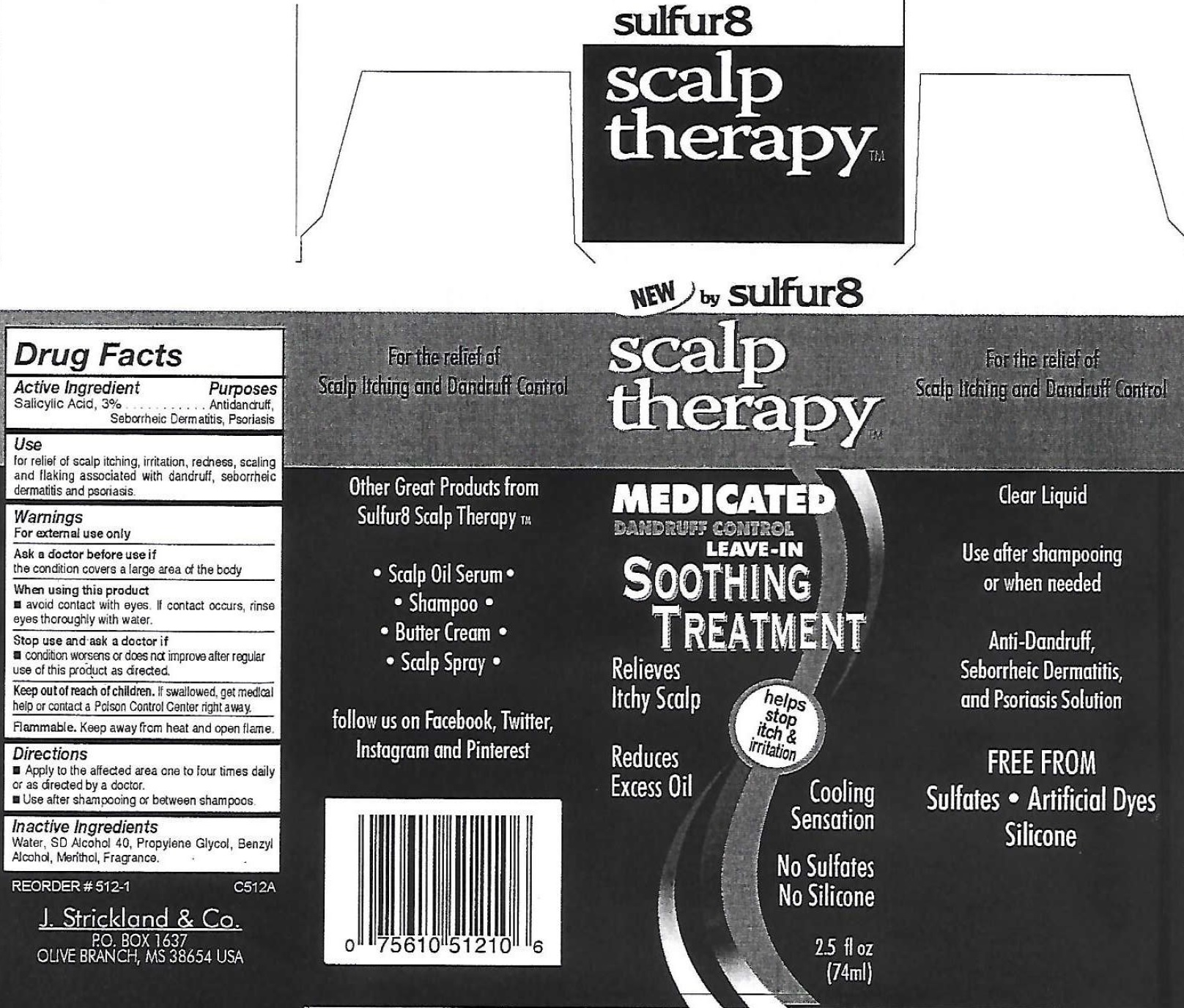 DRUG LABEL: Sulfur 8 Scalp Therapy Medicated Dandruff Control Leave-In Soothing  Treatment
NDC: 12022-033 | Form: SOLUTION
Manufacturer: J. Strickland and Co.
Category: otc | Type: HUMAN OTC DRUG LABEL
Date: 20231021

ACTIVE INGREDIENTS: SALICYLIC ACID 30 mg/1 mL
INACTIVE INGREDIENTS: WATER; PROPYLENE GLYCOL; BENZYL ALCOHOL; MENTHOL

Sulfur 8 Scalp Therapy Medicated Dandruff Control Leave-In Soothing Treatment

Active Ingredient

Salicylic Acid, 2%

Purpose

Antidandruff, Seborrheic Dermatitis, Psoriasis

Use:

for relief of scalp itching, irritation, redness, scaling and flaking associated with dandruff, seborrheic dermatitis, psoriasis.

Warnings

For external use only

Ask a doctor before use

if the condition covers a large area of the body.

When using this product

avoid contact with eyes. If contact, rinse eyes thoroughly with water.

Stop use and consult a doctor if

condition worsens or does not improve after regular use of this product as directed.

Keep out of reach of children.

If swallowed, get medical help or contact a Poison Control Center right away.

Keep away from heat and open flame. Flammable

Directions

Apply to the affected area one to four times daily or as directed by a doctor. Use after shampooing or between shampoos.

Inactive Ingredients

Water, SD Alcohol 40, Propylene Glycol, Benzyl Alcohol, Menthol, Fragrance